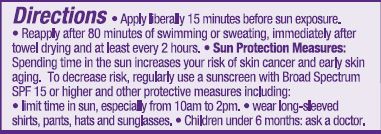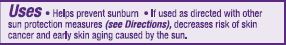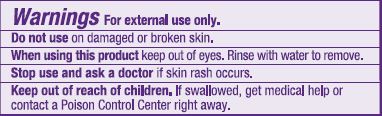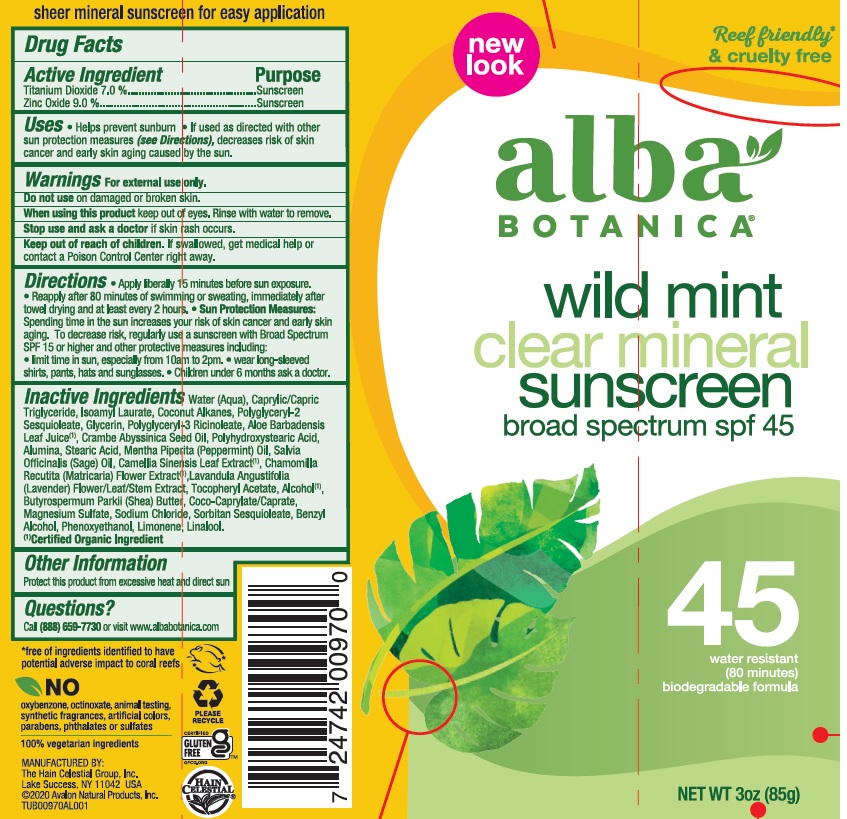 DRUG LABEL: Wild Mint Clear SPF 45
NDC: 61995-1970 | Form: LOTION
Manufacturer: The Hain Celestial Group, Inc
Category: otc | Type: HUMAN OTC DRUG LABEL
Date: 20210412

ACTIVE INGREDIENTS: ZINC OXIDE 9 g/100 g; TITANIUM DIOXIDE 7 g/100 g
INACTIVE INGREDIENTS: COCO-CAPRYLATE/CAPRATE; ALOE VERA LEAF; MEDIUM-CHAIN TRIGLYCERIDES; WATER; POLYGLYCERYL-3 RICINOLEATE; PEPPERMINT OIL; CAMELLIA SINENSIS WHOLE; MATRICARIA CHAMOMILLA FLOWERING TOP; GLYCERYL CAPRYLATE; COCONUT ALKANES; LIMONENE, (+/-)-; LINALOOL, (+/-)-; GLYCERIN; POLYGLYCERYL-2 SESQUIOLEATE; SHEA BUTTER; PHENOXYETHANOL; ALCOHOL; SAGE OIL; SORBITAN OLIVATE; SODIUM CHLORIDE; .ALPHA.-TOCOPHEROL ACETATE, D-; POLYHYDROXYSTEARIC ACID (2300 MW); LAVANDULA ANGUSTIFOLIA FLOWERING TOP; CRAMBE HISPANICA SUBSP. ABYSSINICA SEED OIL; ALUMINUM SULFATE; SORBITAN SESQUIOLEATE; BENZYL ALCOHOL; ISOAMYL LAURATE; STEARIC ACID; MAGNESIUM SULFATE, UNSPECIFIED FORM

Wild Mint Mineral SPF 45 Clear Lotion

ACTIVE INGREDIENT

Titanium Dioxide 7.0%

Zinc Oxide 9.0%

PURPOSE

Sunscreen

INACTIVE INGREDIENT

Water (Aqua), Caprylic/Capric Triglyceride, Isoamyl Laurate, Coconut Alkanes, Polyglyceryl-2 Sesquioleate, Glycerin, Polyglyceryl-3 Ricinoleate, Aloe Barbadensis Leaf Juice (1), Crambe Abyssinica Seed Oil, Polyhydroxystearic Acid, Alumina, Stearic Acid, Mentha Piperita (Peppermint) Oil, Salvia Officinalis (Sage) Oil, Camellia Sinensis Leaf Extract (1), Chamomilla Recutita (Matricaria) Flower Extract (1),Lavandula Angustifolia (Lavender) Flower/Leaf/Stem Extract, Tocopheryl Acetate, Alcohol (1), Butyrospermum Parkii (Shea) Butter, Coco-Caprylate/Caprate, Magnesium Sulfate, Sodium Chloride, Sorbitan Sesquioleate, Benzyl Alcohol, Phenoxyethanol, Limonene, Linalool.

(1) Certified Organic Ingredient